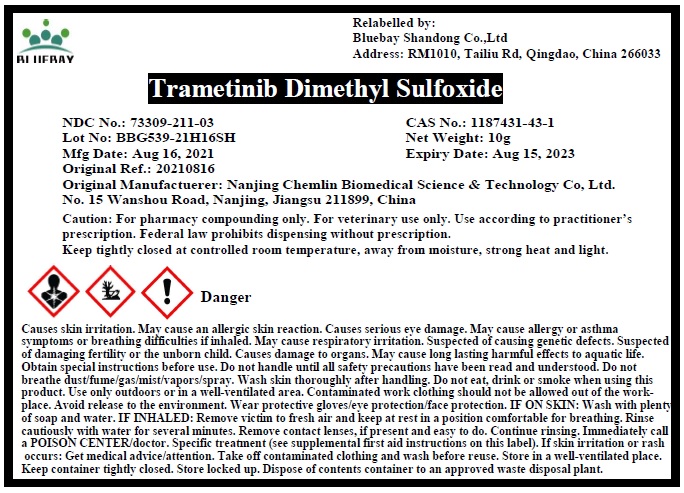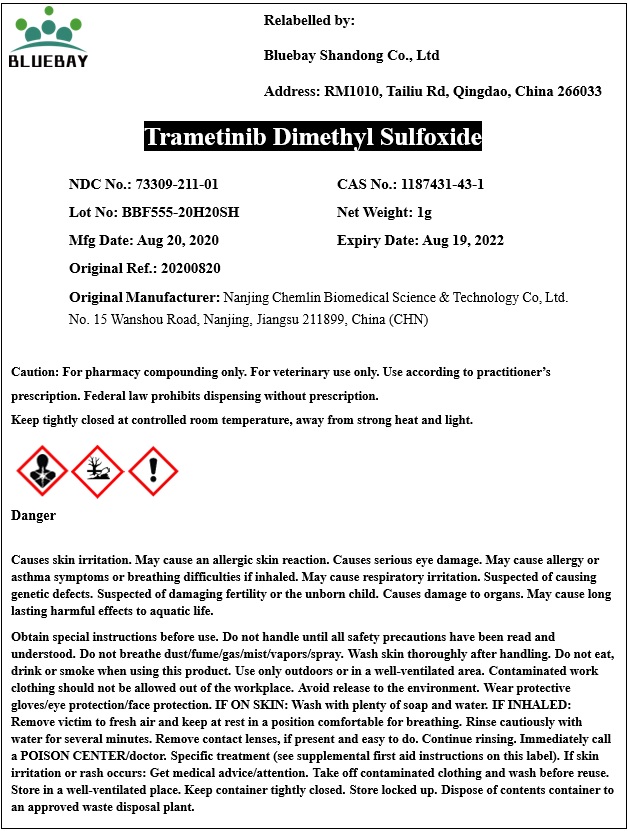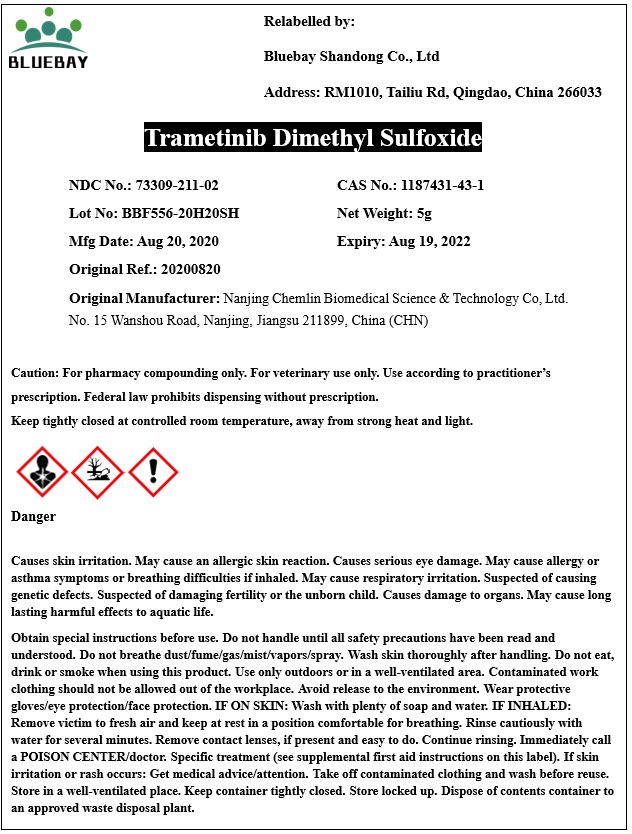 DRUG LABEL: Trametinib Dimethyl Sulfoxide
NDC: 73309-211 | Form: POWDER
Manufacturer: BLUEBAY SHANDONG CO.,LTD
Category: other | Type: BULK INGREDIENT
Date: 20211022

ACTIVE INGREDIENTS: TRAMETINIB DIMETHYL SULFOXIDE 1 g/1 g

Trametinib Dimethyl Sulfoxide